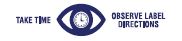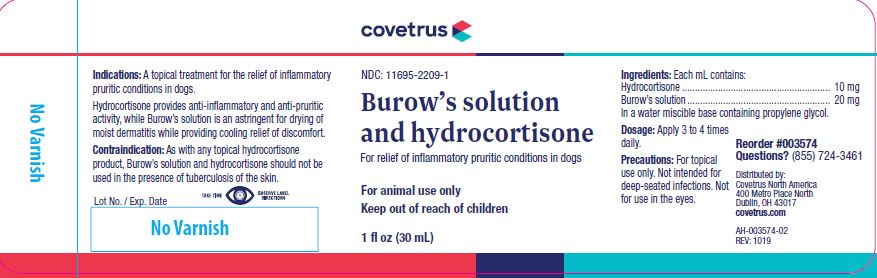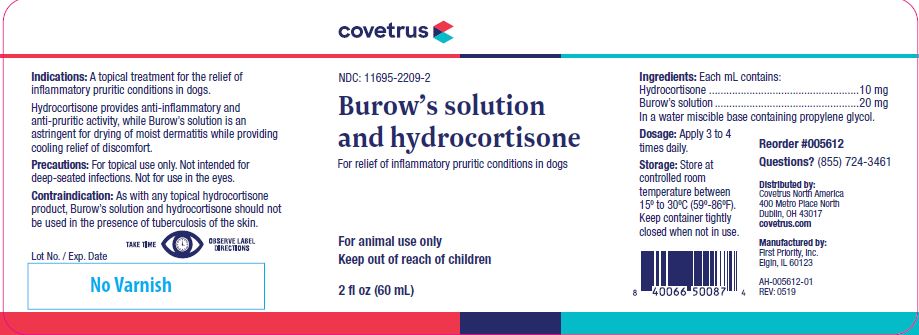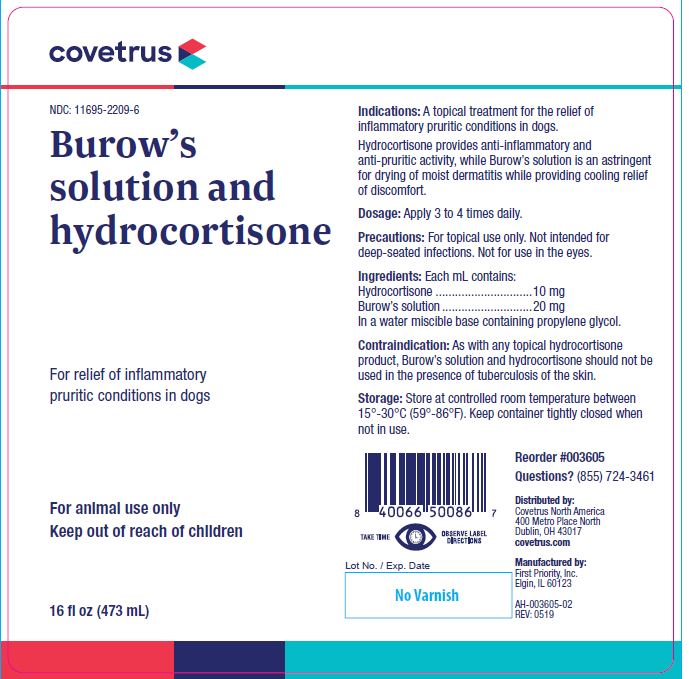 DRUG LABEL: Burows solution and hydrocortisone
NDC: 11695-2209 | Form: LIQUID
Manufacturer: Butler Animal health Supply, LLC dba Covetrus North America
Category: animal | Type: OTC ANIMAL DRUG LABEL
Date: 20221115

ACTIVE INGREDIENTS: HYDROCORTISONE 1.02 mg/1 mL; ALUMINUM ACETATE 0.073 mg/1 mL; ACETIC ACID 0.0624 mg/1 mL

Burow’s solution and hydrocortisone

INFORMATION FOR OWNERS/CAREGIVERS

For relief of inflammatory pruritic conditions in dogs

KEEP OUT OF REACH OF CHILDREN

For animal use only
Keep out of reach of children

Indications:

A topical treatment for the relief of inflammatory pruritic conditions in dogs.

Hydrocortisone provides antiinflammatory and anti-pruritic activity, while Burow’s Solution is an astringent for drying of moist dermatitis while providing cooling relief of discomfort.

Dosage:

Apply 3 to 4 times daily.

Precautions:

For topical use only. Not intended for deep-seated infections. Not for use in the eyes.

Ingredients:

Each mL contains:
Hydrocortisone.....................10 mg
Burow’s solution...................20 mg

INACTIVE INGREDIENT

In a water miscible base containing propylene glycol.

Contraindication:

As with any topical hydrocortisone product, Burow’s solution and hydrocortisone should not be used in the presence of tuberculosis of the skin.

Storage:

Store at controlled room temperature between 15°-30°C (59°-86°F). Keep container tightly closed when not in use.

Net Contents:

1 fl oz (30 mL) Reorder #003574 AH-003574-02 REV: 1019

2 fl oz (60 mL) Reorder #005612 AH-005612-01 REV: 0519

16 fl oz (473 mL) Reorder #003605 AH-003605-02 REV: 0519

INFORMATION FOR OWNERS/CAREGIVERS

Questions? (855) 724-3461

Distributed by:
Covetrus North America
400 Metro Place North
Dublin, OH 43017
covetrus.com

Manufactured by:
First Priority, Inc.
Elgin, IL 60123